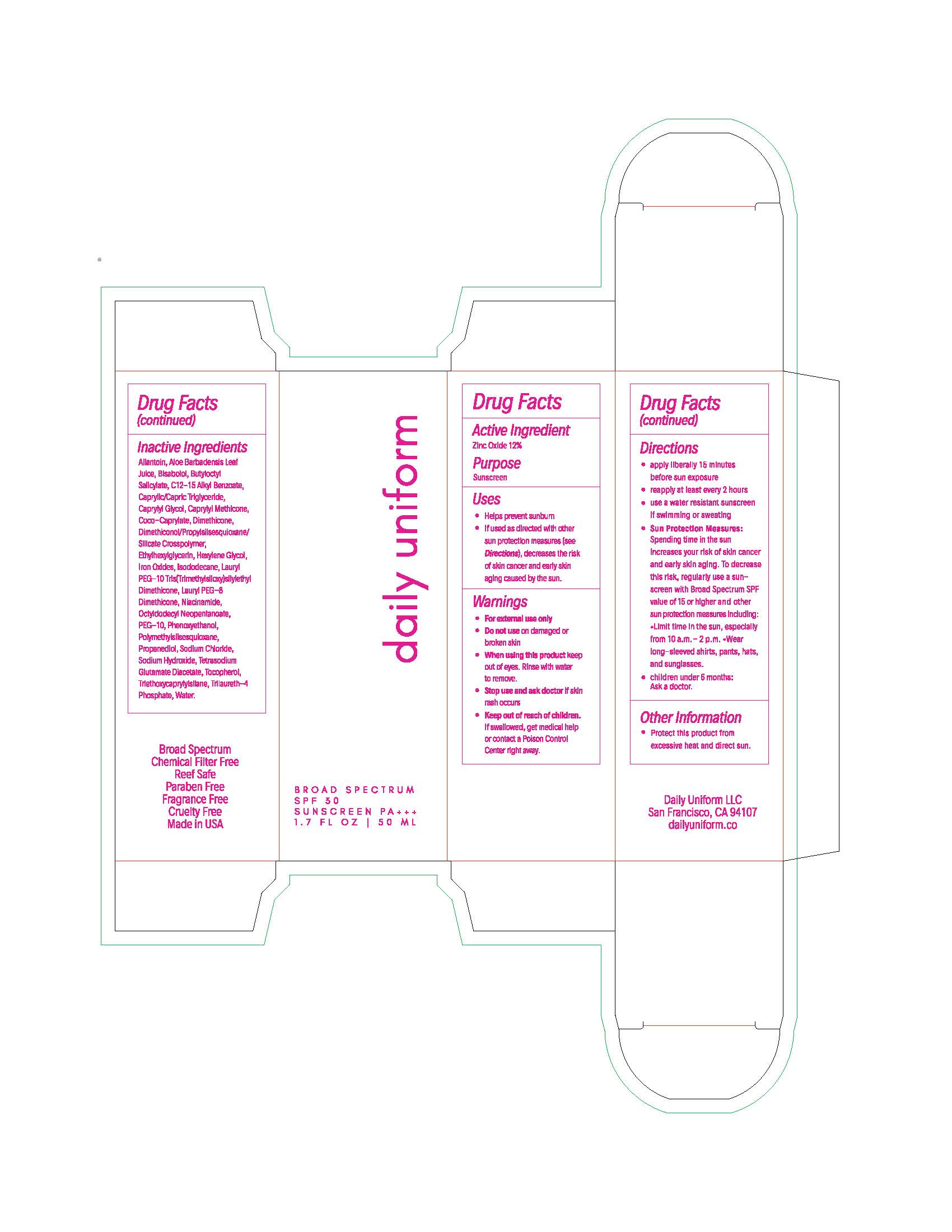 DRUG LABEL: Daily Uniform
NDC: 82766-1095 | Form: LOTION
Manufacturer: Daily Uniform, LLC
Category: otc | Type: HUMAN OTC DRUG LABEL
Date: 20230307

ACTIVE INGREDIENTS: ZINC OXIDE 132 mg/1 mL
INACTIVE INGREDIENTS: TRIETHOXYCAPRYLYLSILANE; FERRIC OXIDE RED; POLYMETHYLSILSESQUIOXANE (11 MICRONS); SODIUM HYDROXIDE; WATER; NIACINAMIDE; ETHYLHEXYLGLYCERIN; HEXYLENE GLYCOL; ALLANTOIN; DIMETHICONOL/PROPYLSILSESQUIOXANE/SILICATE CROSSPOLYMER (450000000 MW); PROPANEDIOL; TETRASODIUM GLUTAMATE DIACETATE; SODIUM CHLORIDE; PHENOXYETHANOL; TOCOPHEROL; TRILAURETH-4 PHOSPHATE; BUTYLOCTYL SALICYLATE; OCTYLDODECYL NEOPENTANOATE; ISODODECANE; .ALPHA.-BISABOLOL, (+)-; FERRIC OXIDE YELLOW; ALKYL (C12-15) BENZOATE; FERROSOFERRIC OXIDE

Daily Uniform